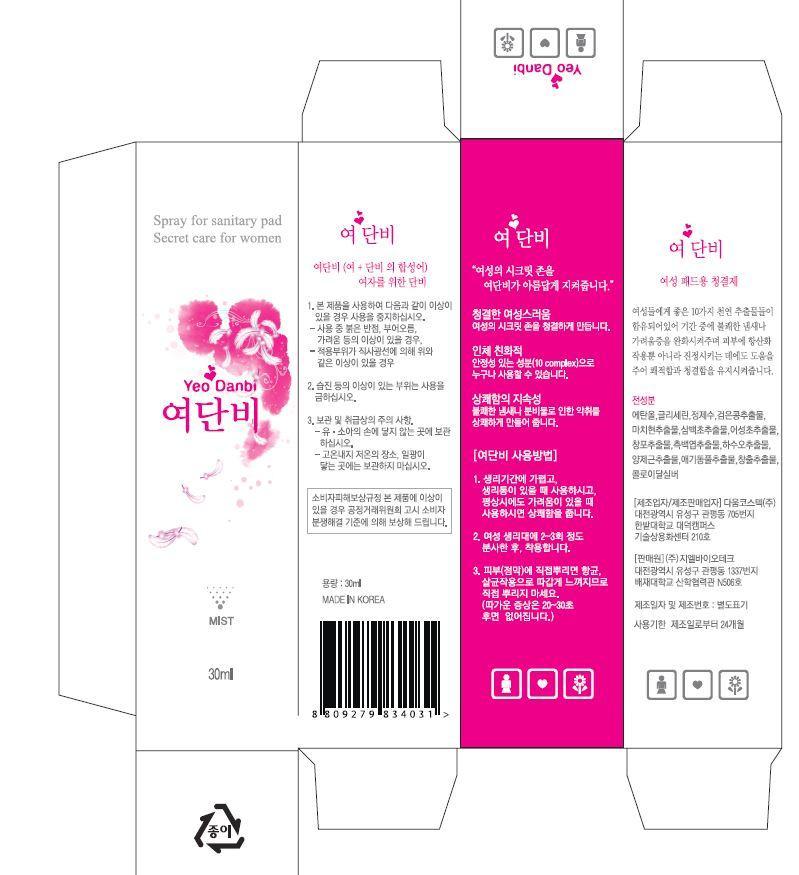 DRUG LABEL: Yeo Danbi
NDC: 69224-3001 | Form: LIQUID
Manufacturer: GL BioTech 
Category: otc | Type: HUMAN OTC DRUG LABEL
Date: 20141017

ACTIVE INGREDIENTS: GLYCERIN 2 g/100 mL
INACTIVE INGREDIENTS: WATER; ALCOHOL

Drug Facts

ACTIVE INGREDIENT

glycerin

INACTIVE INGREDIENT

black bean ext, colloidal silver, iris ext etc

PURPOSE

for itching skin
skin protectant

keep out or reach of the children

INDICATIONS AND USAGE

After spraying it 2 or 3 times into sanitary pads, Please wear it.

WARNINGS

Do not splash it directly to the skin.If you splash it directly to the skin, you feel tingling because of sterilizing effect.The symptoms will clear up after 20 or 30 seconds.

DOSAGE AND ADMINISTRATION

for exernal use only